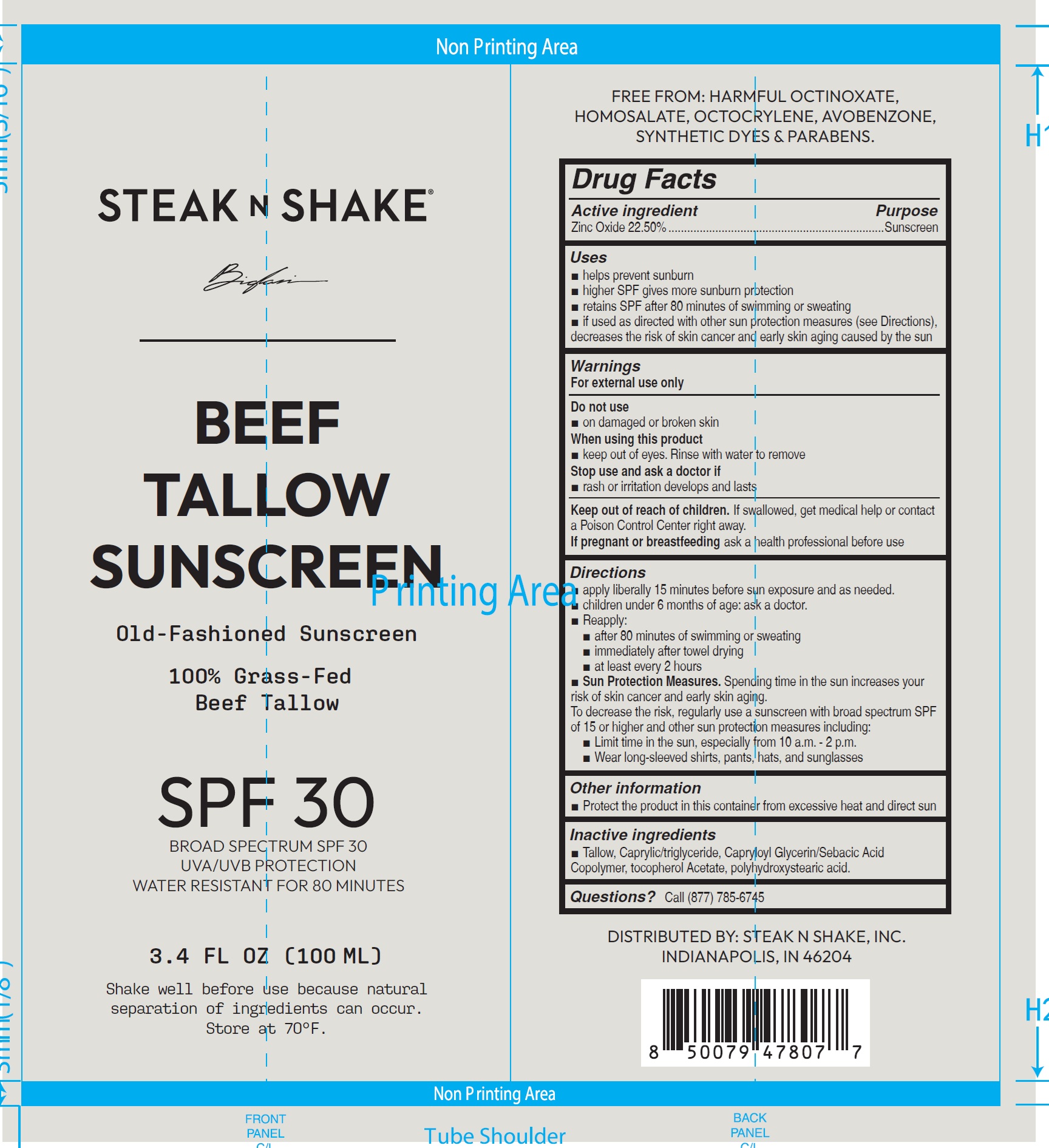 DRUG LABEL: Steak n Shake Beef Tallow Sunscreen SPF 30
NDC: 87420-977 | Form: CREAM
Manufacturer: HRR Enterprises, Inc
Category: otc | Type: HUMAN OTC DRUG LABEL
Date: 20260212

ACTIVE INGREDIENTS: ZINC OXIDE 225 mg/1 mL
INACTIVE INGREDIENTS: TALLOW; TRICAPRILIN; .ALPHA.-TOCOPHEROL ACETATE

Steak n Shake Beef Tallow Sunscreen SPF 30

Active ingredient

Zinc Oxide 22.50%

Purpose

Sunscreen

Uses

- helps prevent sunburn
- higher SPF gives more sunburn protection
- retains SPF after 80 minutes of swimming or sweating
- if used as directed with other sun protection measures (see Directions), decreases the risk of skin cancer and early skin aging caused by the sun

Warnings

For external use only

Do not use

- on damaged or broken skin

When using this product

- keep out of eyes. Rinse with water to remove

Stop use and ask a doctor if

- rash or irritation develops and lasts

Keep out of reach of children.

If swallowed, get medical help or contact a Poison Control Center right away.

If pregnant or breastfeeding

ask a health professional before use

Directions

- apply liberally 15 minutes before sun exposure and as needed.
- children under 6 months of age: ask a doctor.
- Reapply:
- after 80 minutes of swimming or sweating
- immediately after towel drying
- at least every 2 hours
- Sun Protection Measures.Spending time in the sun increases your risk of skin cancer and early skin aging.

To decrease the risk, regularly use a sunscreen with broad spectrum SPF of 15 or higher and other sun protection measures including:

- Limit time in the sun, especially from 10 a.m. - 2 p.m.
- Wear long-sleeved shirts, pants, hats, and sunglasses

Other information

- Protect the product in this container from excessive heat and direct sun

Inactive ingredients

- Tallow, Caprylic/triglyceride, Capryloyl Glycerin/Sebacic Acid Copolymer, tocopherol Acetate, polyhydroxystearic acid.

Questions?

Call (877) 785-6745